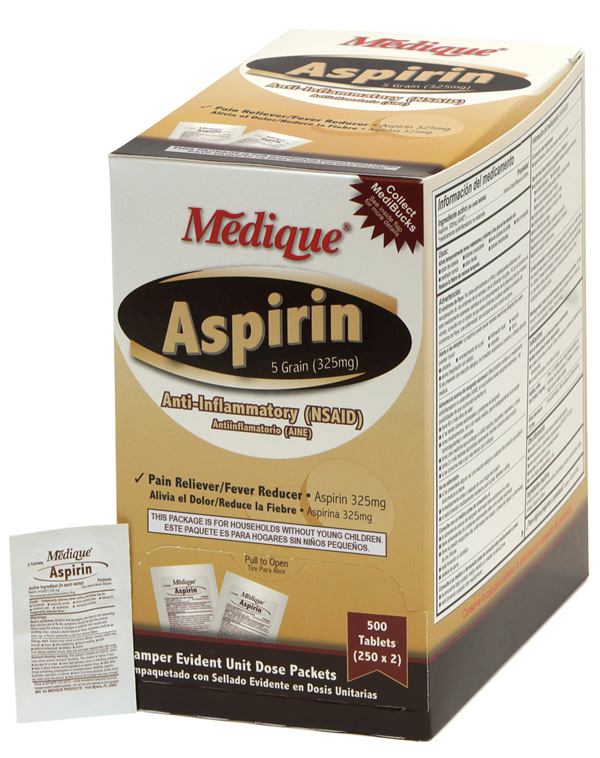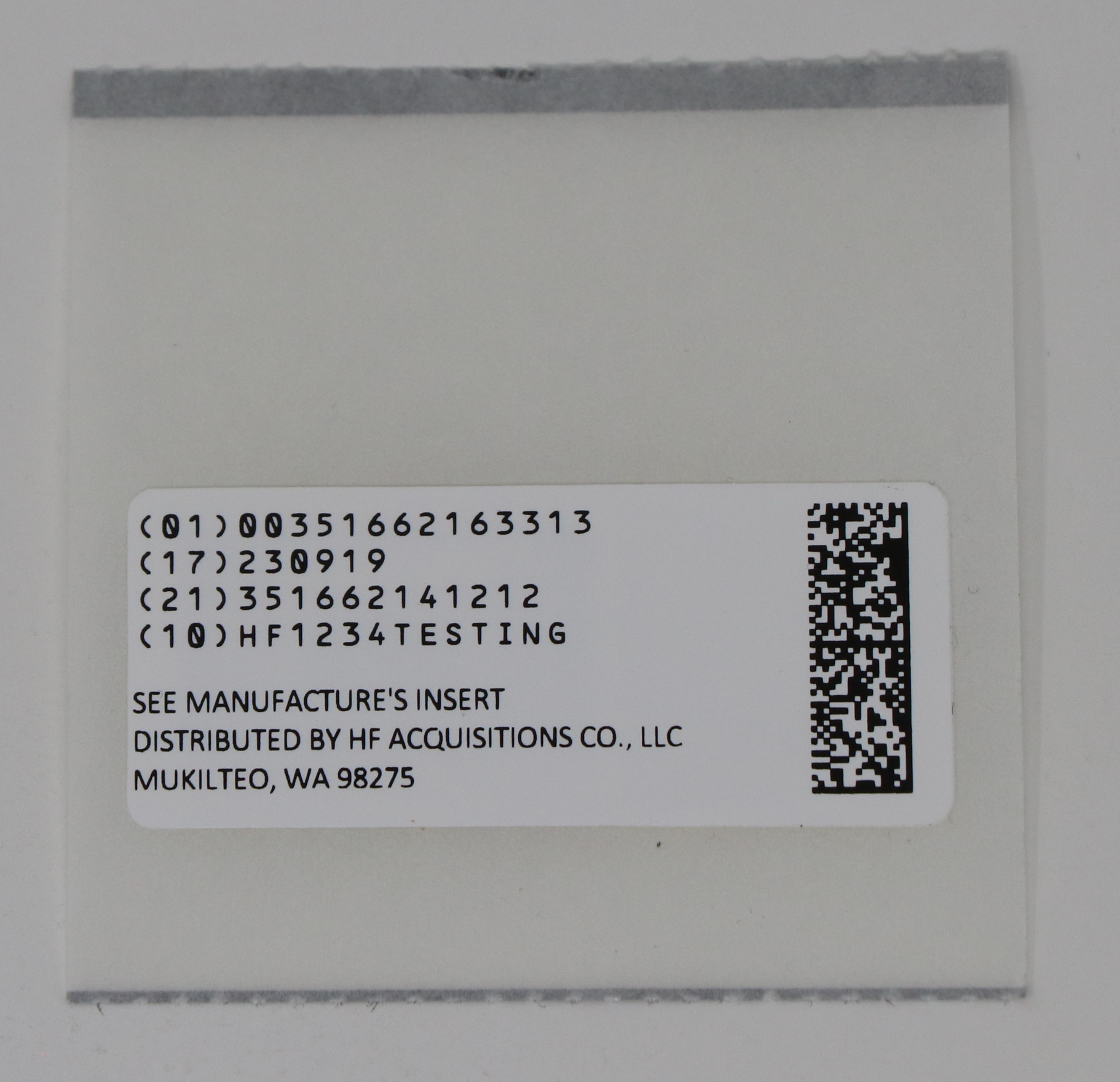 DRUG LABEL: MEDIQUE ASPIRIN
NDC: 51662-1633 | Form: TABLET, FILM COATED
Manufacturer: HF Acquisition Co LLC, DBA HealthFirst
Category: otc | Type: HUMAN OTC DRUG LABEL
Date: 20240329

ACTIVE INGREDIENTS: ASPIRIN 325 mg/1 1
INACTIVE INGREDIENTS: MINERAL OIL; CELLULOSE, MICROCRYSTALLINE; CROSCARMELLOSE SODIUM; STARCH, CORN; HYPROMELLOSES; TITANIUM DIOXIDE

ACTIVE INGREDIENT

Aspirin (NSAID*) 325mg

*nonsteroidal anti-inflammatory drug

PURPOSE

Pain Reliever / Fever Reducer

USES

Temporarily relieves minor aches and pains associated with: headache; muscular aches; minor arthritis pain; backache; common cold; toothache; menstrual cramps; temporarily reduces fever

WARNINGS

Reye's syndrome: Children and teenagers who have or are recovering from chicken pox of flu-like symptoms should not use this product. When using this product, if changes in behavior with nausea and vomiting occur, consult a doctor because these symptoms could be an early sign of Reye's syndrome, a rare but serious illness.

Allergy Alert: Aspirin may cause a severe allergic reaction which may include: hives, skin reddening, facial swelling, rash, asthma (wheezing), blisters, shock. If an allergic reaction occurs, stop use and seek medical help right away.

Stomach bleeding warning: This contains an NSAID, which may cause severe stomach bleeding. The change is higher if you: are age 60 or older; have had stomach ulcers or bleeding problems; take a blood thinner (anticoagulant) or steroid drug; take other drugs containing prescription or nonprescription NSAIDs (aspirin, ibuprofen, naproxen, or others), have 3 or more alcoholic drinks everyday while using this product, take more for a longer time than directed

DO NOT USE- ASPIRIN

Do not use if you have ever had an allergic reaction to any other pain reliever/fever reducer; right before or after heart surgery; if you are taking a prescription drug for gout, diabetes or arthritis.

Ask a doctor before use if: stomach bleeding warning applies to you; you have a history of stomach problems such as heartburn; you have high blood pressure, heart disease, liver cirrhosis or kidney disease; you are taking a diuretic.

Ask a doctor or pharmacist before use if you are: under a doctor's care for any serious condition; taking any other drug.

When using this product: Take with food or milk if stomach upset occurs.

STOP USE AND ASK DOCTOR- ASPIRIN

Stop Use and ask a Doctor if:

You experience any of the following signs of stomach bleeding, you feel faint, vomit blood, have bloody or black stools, have stomach pain that does not get better, pain gets worse or lasts more than 10 days, fever gets worse or lasts more than 3 days, you have difficulty swallowing, if ringing in the ears or loss of hearing occurs, redness or swelling is present in painful areas, or any new symptoms appear.

If pregnant or breast-feeding, ask a health professional before use. It is especially important not to use aspirin during the last 3 months of pregnancy unless directed to do so by a doctor because it may cause problems in the unborn child or complications during delivery.

Keep out of reach of Children. In case of overdose, get medical help or contact a poison control center right away.

DIRECTIONS

Do not use more than directed - the smallest effective dose should be used.

Drink a full glass of water with each dose.

Do not take longer than 10 days, unless directed by a doctor.

Adults and Children (12 years and older): take 1 or 2 tablets with water every 4 hours as needed. Do not take more then 12 tablets in 24 hours, or as directed by a doctor.

Children under 12 years: Do not give to children under 12 years of age.

Avoid excessive heat and humidity, do not use any open or torn packets.

DOSAGE AND ADMINISTRATION

Aspirin (NSAID*) 325mg

Do not use more than directed - the smallest effective dose should be used.

Drink a full glass of water with each dose.

Do not take longer than 10 days, unless directed by a doctor.

Adults and Children (12 years and older): take 1 or 2 tablets with water every 4 hours as needed. Do not take more then 12 tablets in 24 hours, or as directed by a doctor.

Children under 12 years: Do not give to children under 12 years of age.

Avoid excessive heat and humidity, do not use any open or torn packets.

Do not use more than directed - the smallest effective dose should be used.

Drink a full glass of water with each dose.

Do not take longer than 10 days, unless directed by a doctor.

Adults and Children (12 years and older): take 1 or 2 tablets with water every 4 hours as needed. Do not take more then 12 tablets in 24 hours, or as directed by a doctor.

Children under 12 years: Do not give to children under 12 years of age.

Avoid excessive heat and humidity, do not use any open or torn packets.

KEEP OUT OF REACH OF CHILDREN

INACTIVE INGREDIENT

MINERAL OIL
CELLULOSE, MICROCRYSTALLINE
CROSCARMELLOSE SODIUM
HYPROMELLOSES
TITANIUM DIOXIDE
STARCH, CORN